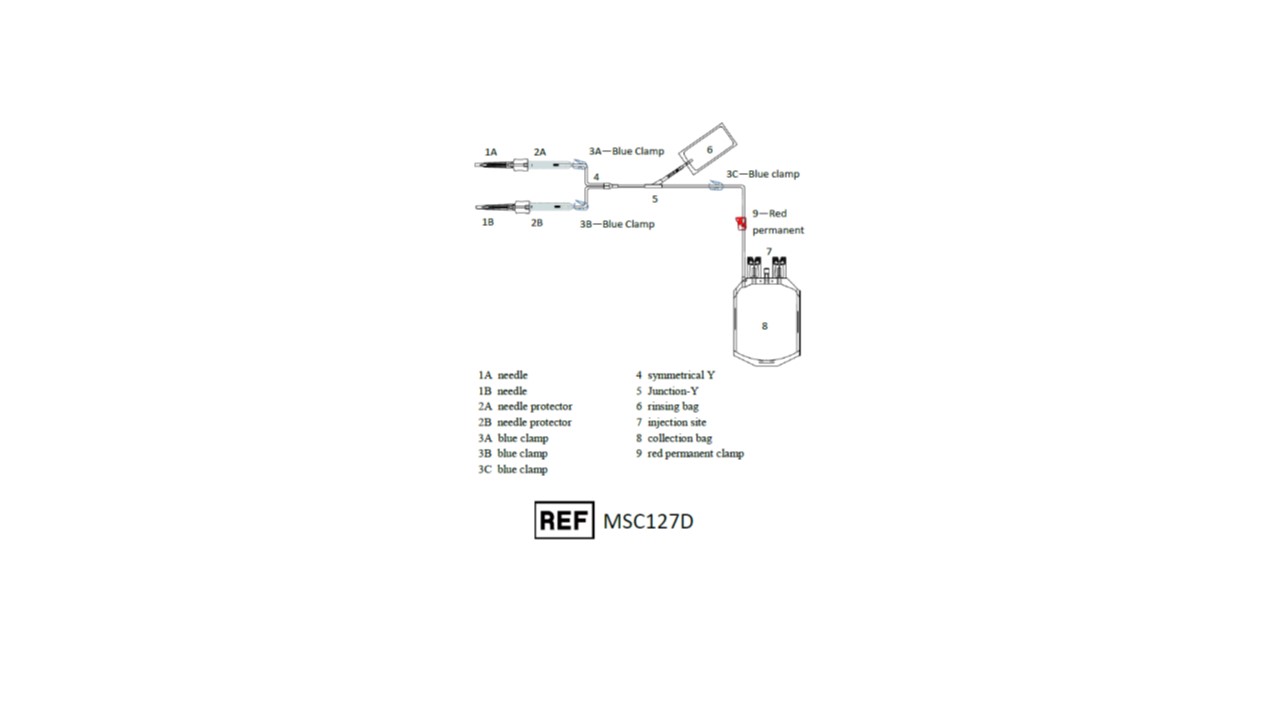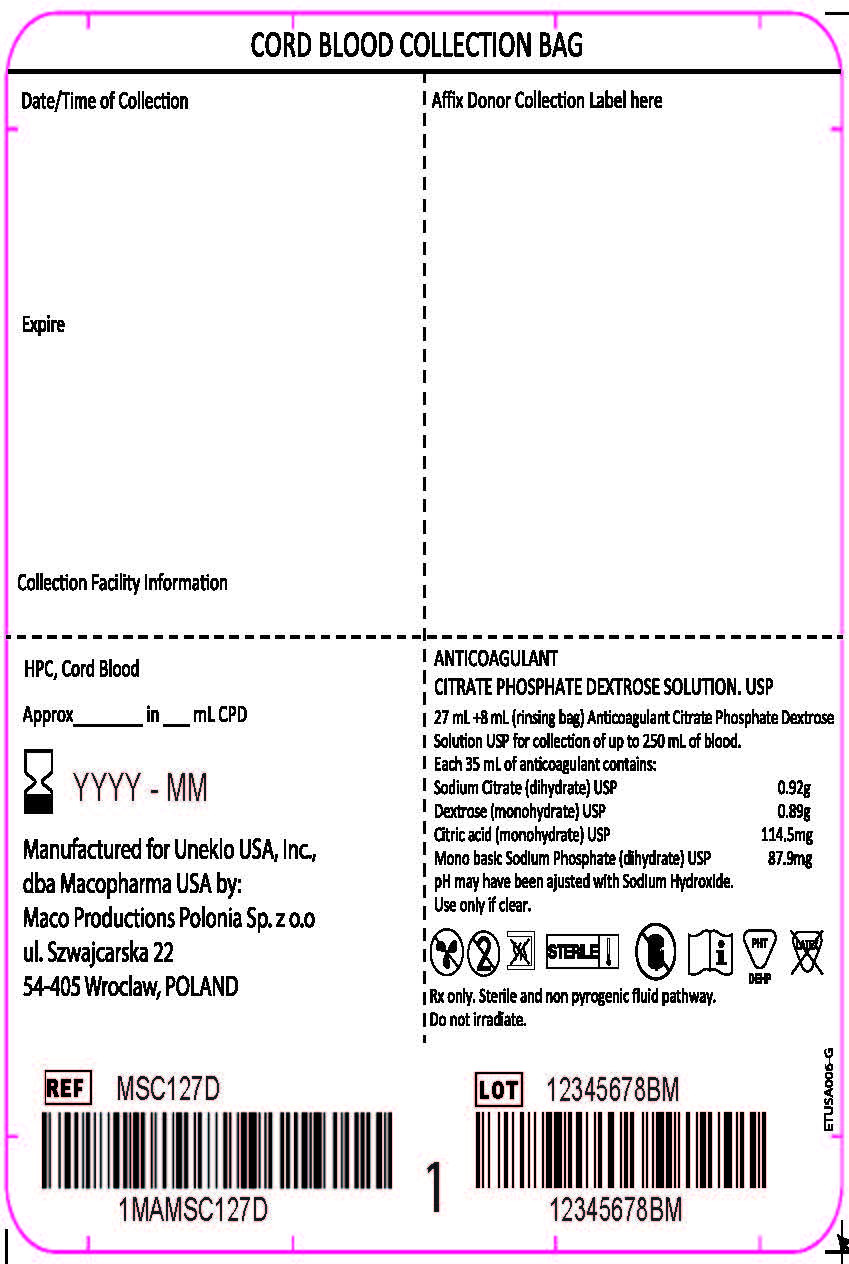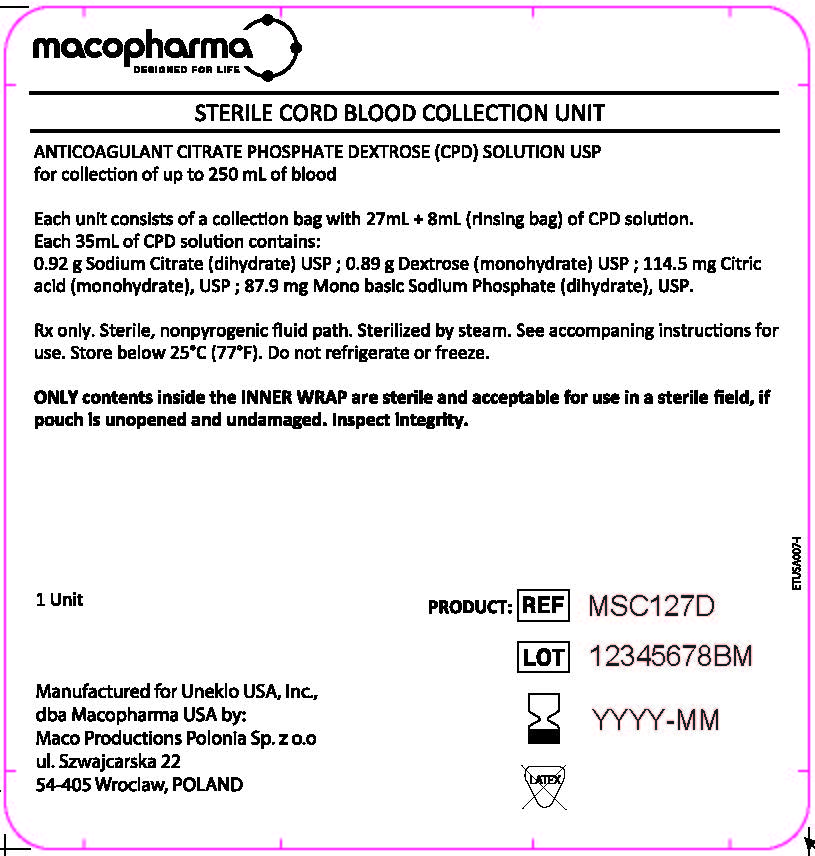 DRUG LABEL: Sterile Cord Blood Collection Unit (MSC127D)
NDC: 14498-003 | Form: INJECTION, SOLUTION
Manufacturer: Maco Productions
Category: prescription | Type: HUMAN PRESCRIPTION DRUG LABEL
Date: 20251218

ACTIVE INGREDIENTS: SODIUM CITRATE 0.92 g/35 mL; DEXTROSE MONOHYDRATE 0.89 g/35 mL; CITRIC ACID MONOHYDRATE 114.5 mg/35 mL; SODIUM PHOSPHATE, MONOBASIC, DIHYDRATE 87.9 mg/35 mL

Sterile Cord Blood Collection Unit (MSC127D)

MACO BIOTECH Collection - Sterile Cord Blood Collection Unit (MSC127D)

The MSC127D Sterile Cord Blood Collection Unit consists of 300 mL collection bag containing 27 mL of Anticoagulant Citrate Phosphate Dextrose Solution USP (CPD), a 40 mL rinsing bag containing 8 mL of CPD and two 12 gauge needles with a protective shield (SECUVAM) for the used needle.

Sterile, non-pyrogenic fluid path. Sterilized by steam.

Rx only.

This product is not made with natural rubber latex.

INDICATIONS AND USAGE

MSC127D - For collection of up to 250 mL of umbilical cord blood. Use aseptic technique.

WARNINGS

- Avoid contact with sharp objects.
- Do not irradiate collected cord blood or components.
- Making multiple punctures of the umbilical cord to increase collection volume may increase the risk of contamination.

PRECAUTIONS

- DO NOT use if the overwraps or bags show any signs of alteration.
- This is a single use sterile kit: under no circumstances should it be reused.
- For optimal cord blood quality it is recommended to maintain the cord blood at an ambient temperature (18-26°C / 64.4-78.8°F) or cold temperature (4-12°C / 39.2-53.6°F) and process within 48 hours of collection.^1,2,3

If the collection volume is less than 60 mL, the cord blood should be processed withing 24 hours of collection.

HOW SUPPLIED

MSC127D Sterile Cord Blood Collection Unit contains:

- 300 mL collection bag containing 27 mL CPD
- 40 mL rinsing bag contaning 8 mL CPD
- 2-12 gauge needles with a protective shield (SECUVAM) for used needle
- Graduation label as visual aid to approximate the volume

INSTRUCTIONS FOR USE Carefully Read All the Instructions Before Use

Representative Product Drawing

I. PREPARATION

- Before use, verify the integrity of the collection unit (overwrap, outlet ports, tubing...).
- Only contents inside the inner wrap are sterile and acceptable for use in a sterile field if pouch is unopened and undamaged.

II. COLLECTION PROCEDURE

- Close all clamps 3A, 3B and 3C (clamp 9 should remain open).
- After clamping and sectioning of the umbilical cord, place the collection bag on a mixer and perform a venipuncture at lower end of the umbilical cord with first needle 1A.

Note: Umbilical venipunctures can be done before or after the expulsion of the placenta according to your local procedures.

3. Open clamps 3A and 3C.

4. Stimulate cord blood flow by massaging the cord from the top downward to increase volume of collection.

5. When collection is completed, close clamps 3A and 3C.

6. Remove needle 1A and slide down SECUVAM 2A (needle protector) over needle 1A.

7. If necessary, perform a second umbilical venipuncture on the upper part of the umbilical cord (near the mother).

[See Warnings]:

a. Open clamps 3B and 3C.

b. Perform venipuncture on the umbilical cord using other needle 1B.

c. When collection is completed, close clamps 3B and 3C.

d. Remove needle 1B and slide down SECUVAM 2B (needle protector) over needle 1B.

III. RINSING OF COLLECTIONLINE

- Open clamp 3C.
- Snap the break-away cannula on top of rinsing bag 6.
- Roll up bag 6 on itself to empty 8 mL of anticoagulant (CPD) in the tubing to push the cord blood remaining in the tubing into the collection bag. Do not strip the tubing.
- Close clamp 3C.
- Proceed to section V END OF COLLECTION if collection volume is less than 200 mL. For collection volumes greater than 200 mL, proceed to section IV ADDITION OF ANTICOAGULANT INTO THE COLLECTION BAG.

IV. ADDITION OF ANTICOAGULANT INTO THE COLLECTION BAG

Use this step only for collection volumes greater than 200 mL.

- Seal the tubing above the Y junction 5.
- Move clamp 3C near to Y junction 5.
- Using a blood stripper, strip the tubing from Y junction 5 towards the collection bag 8 expelling the anticoagulant in the tubing into collection bag 8.
- Repeat this operation 3 times.
- Mix collection bag 8.
- Close clamp 3C.
- Proceed to section V END OF COLLECTION.

V. END OF COLLECTION

- Close clamp 9 to secure th collection.
- Seal the tubing between clamp 9 and collection bag 8.
- Fill in collection volume and CPD volume on the collection bag label. The amount of CPD is as follows:

a. 27 mL - if no additional CPD is added.

b. 35 mL - if additional 8 mL CPD from rinsing bag is added to the collection bag as directed in section IV.

4. For optimal cord blood quality, maintain the cord blood at an ambient temperature (18-26°C / 64.4-78.8°F) or cold temperature (4-12°C / 39.2-53.6°F).

VI. CONTACT INFORMATION

Manufactured for United States of America (U.S.A.) and Canada by Maco Productions Polonia, Sp. z o.o.

ul. Szwajcarska 22, 54-405 Wroclaw, POLAND

+48 71 37 60 110

For consumer information contact:

- For the U.S.A.: Distributed by Uneklo USA, Inc. dba Macopharma USA

3075 Breckinridge Boulevard, Suite 405, Duluth, GA 30096, USA

(770) 270-6867

- For Canada: Distributed by Macopharma Canada

1200 McGill College, Suite 1715, Montreal (Quebec) H3B 4G7

(514) 866-2222

VII. REFERENCES

- Pope, B. Mitsakos, K., Bilgin, A., Hokin, B. and Grant, R.: Predicting overall viability of cord blood harvests. Transfusion 2012:52:1079-1085
- Salge-Bartels U. Huber. M, Kleiner K, Volkers P, Seitz R, Heiden M: Evaluation of Quality Parameters for Cord Blood Donations, Transfus Med Hemother 2009; 36:317-324
- Prof. Dr. Kogler, Jose Carreras CBB, medical center, University of Duesseldorf: General information on the institution and the production facility of the Jose Carreras Cord Blood Bank. 2014

LABELS

Collection Bag Label

Overwrap Label

REF MSC127D